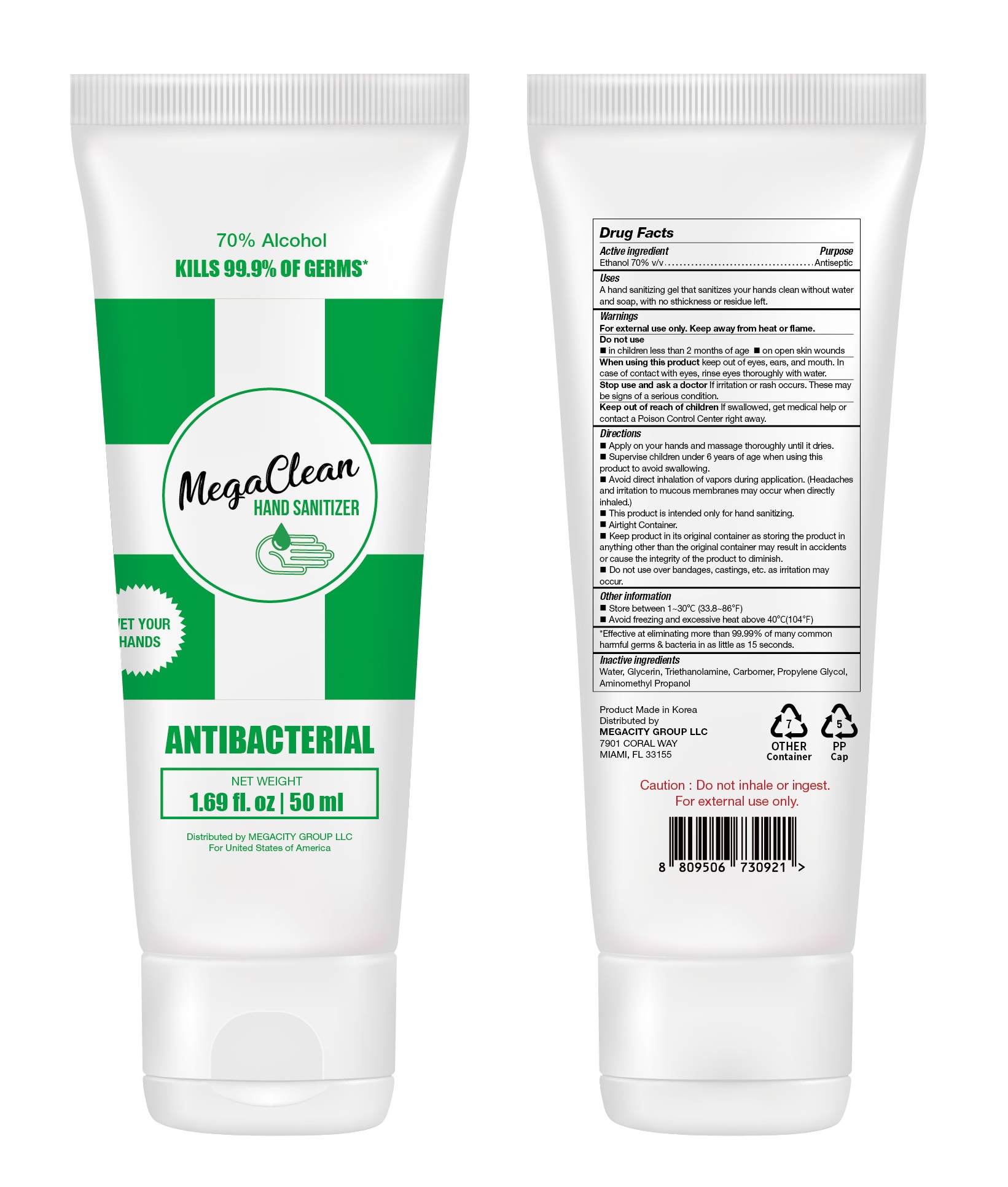 DRUG LABEL: MegaClean HAND SANITIZER
NDC: 77799-057 | Form: GEL
Manufacturer: MEGACITY GROUP LLC
Category: otc | Type: HUMAN OTC DRUG LABEL
Date: 20200531

ACTIVE INGREDIENTS: ALCOHOL 35 mL/50 mL
INACTIVE INGREDIENTS: AMINOMETHYLPROPANOL; GLYCERIN; WATER; PROPYLENE GLYCOL; TROLAMINE; CARBOMER HOMOPOLYMER, UNSPECIFIED TYPE

MegaClean HAND SANITIZER 50 mL : Tube : 77799-057-01